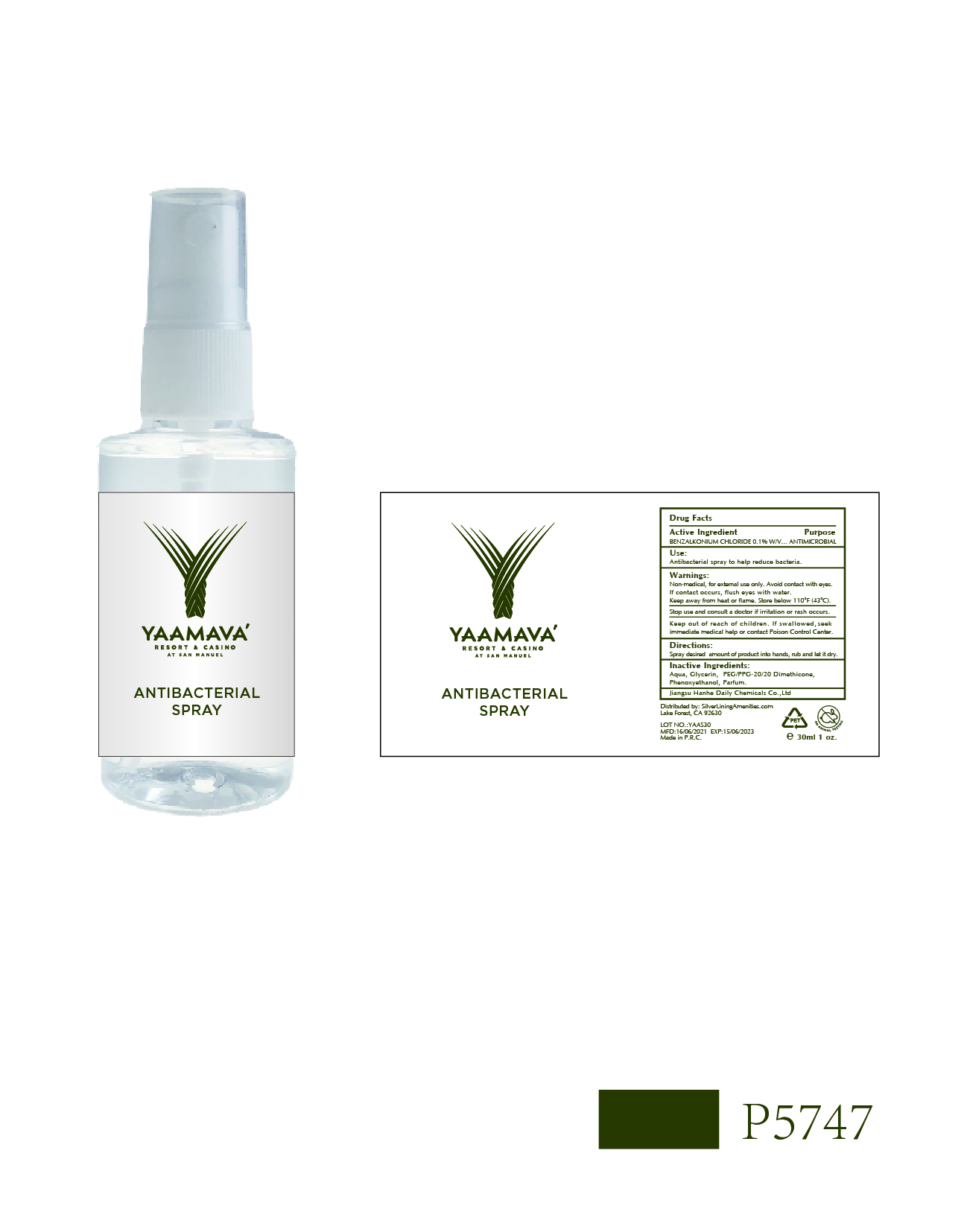 DRUG LABEL: YAAMAVA Antibacterial
NDC: 73027-219 | Form: SPRAY
Manufacturer: JIANGSU HANHE DAILY CHEMICALS CO., LTD.
Category: otc | Type: HUMAN OTC DRUG LABEL
Date: 20211102

ACTIVE INGREDIENTS: BENZALKONIUM CHLORIDE 0.1 g/100 mL
INACTIVE INGREDIENTS: GLYCERIN; PEG/PPG-20/20 DIMETHICONE; WATER; PHENOXYETHANOL

73027-219 Yaamava Spray

Active Ingredient

Benzalkonium Chloride 0.1% w/v

Purpose

Antimicrobial

Use

Antibacterial spray to help reduce bacteria

Warnings

Non Medical. For external use only.

Avoid contact with eyes. If contact occurs, flush eyes with water

Keep away from heat or flame. Store below 110F (43C)

Stop use and consult a doctor if irritation or rash occurs.

Keep out of reach of children. If swallowed, seek immediate medical help or contact a Poison Control Center

Directions

- Spray desired amount of product into hands, rub and let dry

Inactive ingredients

Water, Glycerin, PEG/PPG-20/20 Dimethicone, Phenoxyethanol, Parfume